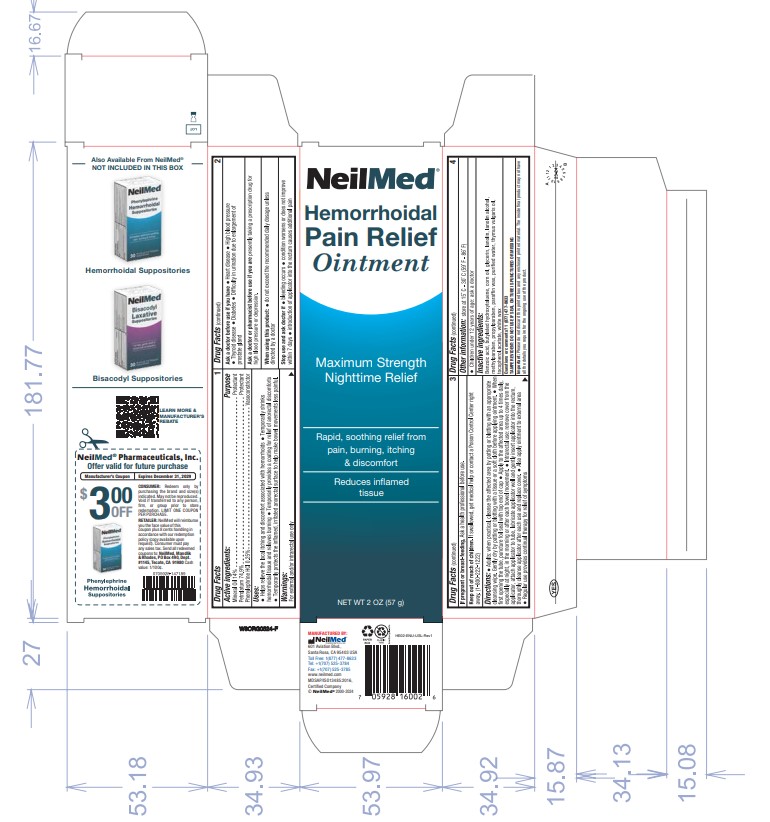 DRUG LABEL: Hemorrhoidal Pain Relief
NDC: 13709-334 | Form: OINTMENT
Manufacturer: Neilmed Pharmaceuticals Inc.
Category: otc | Type: HUMAN OTC DRUG LABEL
Date: 20250611

ACTIVE INGREDIENTS: PETROLATUM 749 mg/1 g; MINERAL OIL 140 mg/1 g; PHENYLEPHRINE HYDROCHLORIDE 2.5 mg/1 g
INACTIVE INGREDIENTS: METHYLPARABEN; PARAFFIN; WATER; THYMUS VULGARIS (THYME) OIL; LANOLIN; PROPYLPARABEN; GLYCERIN; BENZOIC ACID; BUTYLATED HYDROXYTOLUENE; ALPHA-TOCOPHEROL ACETATE; LANOLIN ALCOHOL; WHITE WAX; CORN OIL

Hemorrhoidal Pain Relief Ointment

Drug Facts

Active Ingredients:

Mineral Oil 14%

Petrolatum 74.9%

Phenylephrine HCl 0.25%

Drug Facts:

Purpose

Protectant

Protectant

Vasoconstrictor

Uses:

- Helps relieve the local itching and discomfort associated with hemorrhoids
- Temporarily shrinks hemorrhoidal tissue and relieves burning
- Temporarily provides a coating for relief of anorectal discomforts
- Temporarily protects the inflamed, irritated anorectal surface to help make bowel movements less painful

Warnings:

For external and/or intrarectal use only

Ask a doctor before use if you have:

- Heart disease
- High blood pressure
- Thyroid disease
- Diabetes
- Difficulty in urination due to enlargement of prostate gland

Ask a doctor or pharmacist before use if you are:

Presently taking a prescription drug for high blood pressure or depression

When using this product:

- Do not exceed the recommended daily dosage unless directed by a doctor

Stop use and ask doctor if:

- Bleeding occurs
- Condition worsens or does not improve within 7 days
- Introduction of applicator into the rectum causes additional pain

If pregnant or breast-feeding:

Ask a health professional before use.

Keep out of reach of children.

If swallowed, get medical help or contact a Poison Control Center right away. (1-800-222-1222)

Directions:

- Adults: When practical, cleanse the affected area by patting or blotting with an appropriate cleansing wipe. Gently dry by patting or blotting with a tissue or a soft cloth before applying ointment.
- When first opening the tube, puncture foil seal with top end of cap.
- Apply to the affected area up to 4 times daily, especially at night, in the morning or after each bowel movement.
- Intrarectal use: Remove cover from the applicator, attach applicator to tube, lubricate applicator well and gently insert applicator into the rectum, thoroughly cleanse applicator after each use and replace cover.
- Also apply ointment to external area.
- Regular use provides continual therapy for relief of symptoms.

Other Information:

Store at 15°C – 30°C (59°F – 86°F)

- Children under 12 years of age: ask a doctor

Inactive ingredients:

Benzoic acid, butylated hydroxytoluene, corn oil, glycerin, lanolin, lanolin alcohol, methylparaben, propylparaben, paraffin wax, purified water, thymus vulgaris oil, tocopherol, acetate, white wax

Questions or comments?

1 (877) 477-8633

TAMPER EVIDENT: DO NOT USE IF SEAL ON TUBE IS PUNCTURED OR MISSING

Important:

Please do not discard this printed box and any enclosed printed material. The inside final product may not have all the details you require for the ongoing use of the product.